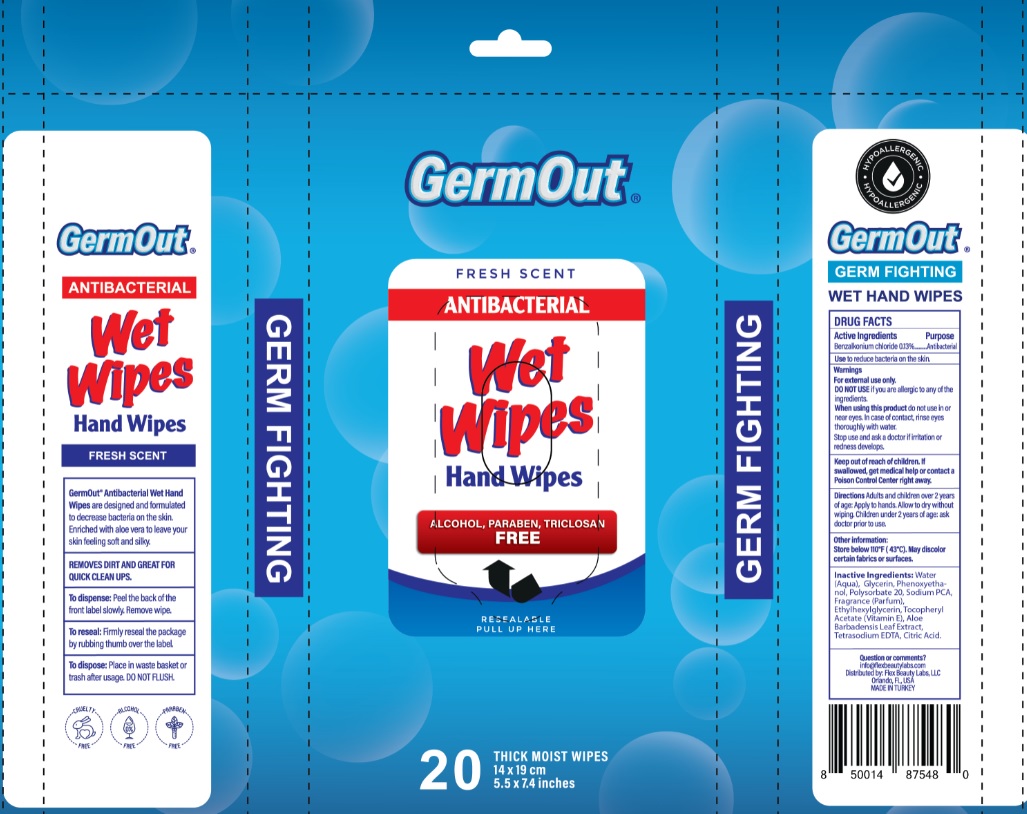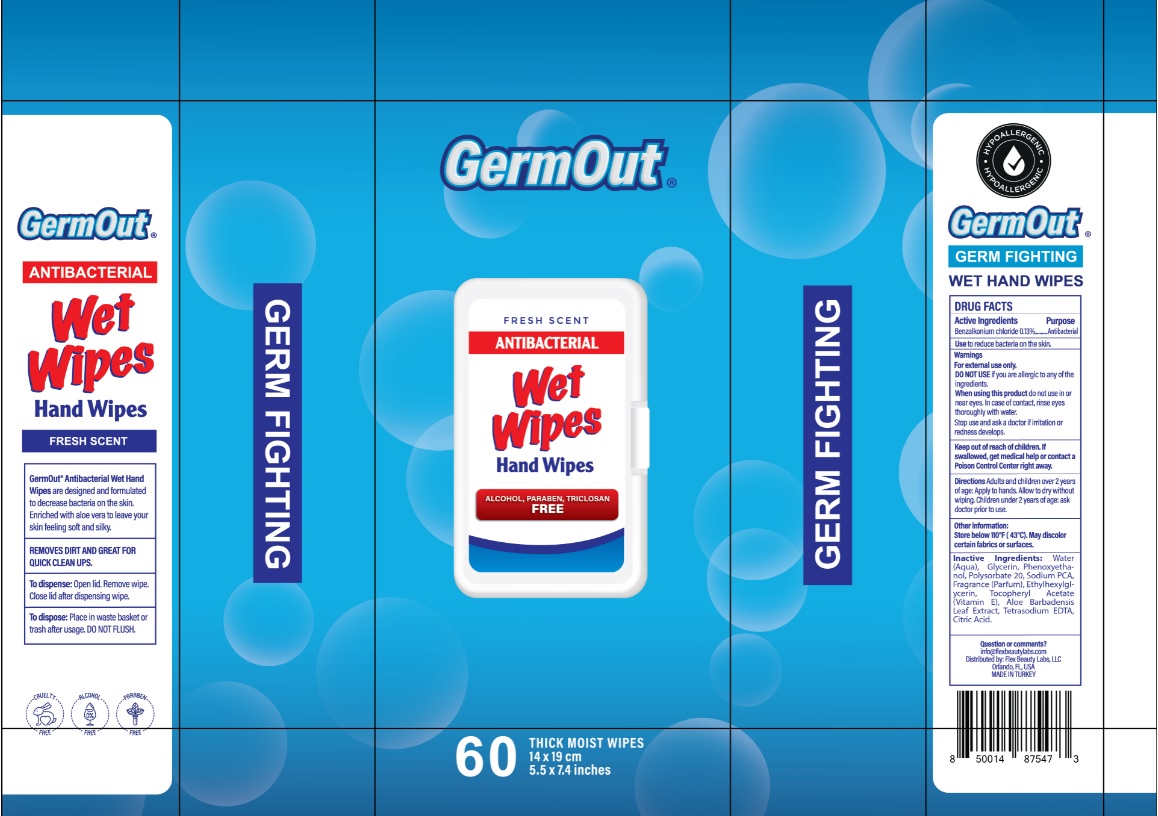 DRUG LABEL: Antiseptic Wipes
NDC: 72308-015 | Form: CLOTH
Manufacturer: Flex Beauty Labs
Category: otc | Type: HUMAN OTC DRUG LABEL
Date: 20200623

ACTIVE INGREDIENTS: BENZALKONIUM CHLORIDE 0.0013 mg/100 mg
INACTIVE INGREDIENTS: WATER; GLYCERIN; SODIUM COCOAMPHOACETATE; ALOE VERA LEAF; .ALPHA.-TOCOPHEROL ACETATE; POLYSORBATE 20; EDETATE SODIUM; PHENOXYETHANOL; METHYLPARABEN; ETHYLHEXYLGLYCERIN; POTASSIUM SORBATE; CITRIC ACID MONOHYDRATE

Germout- Wet Wipes Antibaterial

Active ingredients

Benalkonium chloride (0.13%)

Purpose

Antibacterial

Use

Use to reduce bacteria on the skin

Warnings

For external use only

Do not use if you are allegic to any of the ingredients.

When using this product do not use in or near eyes.

In cases of contact, rinse eyes thoroughly with water.

Stop use and ask a doctor if irritation or redness develops.

Keep out of reach of children.

If swallowed, get medical help or contqact a Poison Control Center right away

Directions:

- Adults and children over 2 yeas of age:Apply to hands. Allow to dry without wioing.
- Children under 2 year of age:ask doctor prior to use

Inactive ingredients

water, glycerin, sodium PCA, Aloe barbadensis leaf juice, fragrance, polysorbate 20, tetrasodium EDTA, phenoxyethanol, ethylhexylglycerin, citric acid

principal display panel

60 WIPES

14 X 19 cm

5.5 IN X 7.4 IN

20 WIPES

14 X 19 cm

5.5 IN X 7.4 IN